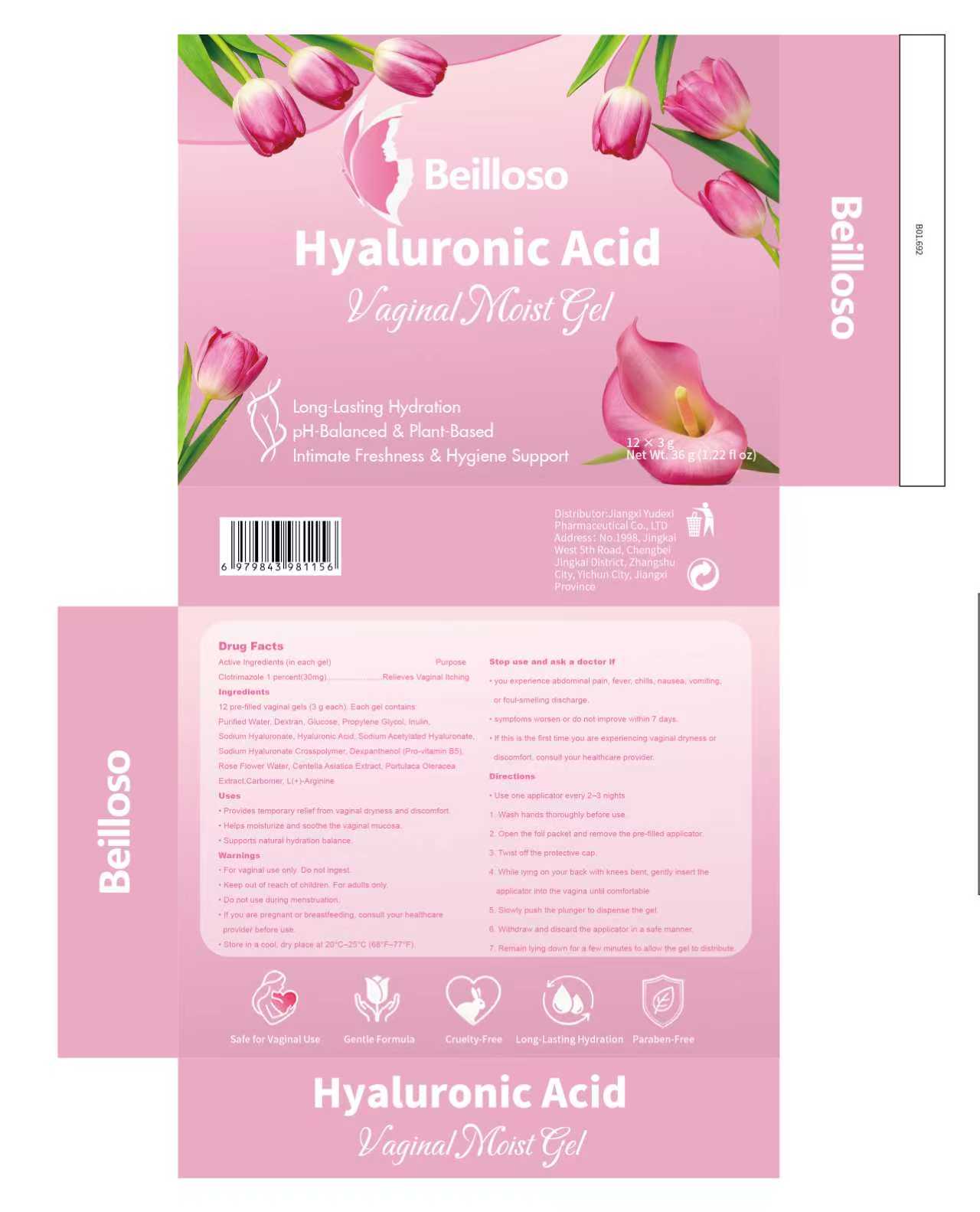 DRUG LABEL: Beilloso Hyaluronic Acid
NDC: 85248-136 | Form: CREAM
Manufacturer: Jiangxi Yudexi Pharmaceutical Co., LTD
Category: otc | Type: HUMAN OTC DRUG LABEL
Date: 20260209

ACTIVE INGREDIENTS: CLOTRIMAZOLE 1 g/100 g
INACTIVE INGREDIENTS: PROPYLENE GLYCOL; SODIUM HYALURONATE; ROSA RUGOSA FLOWER BUD; TARAXEROL; HYALURONIC ACID; ARGININE; SODIUM ACETYLATED HYALURONATE; CARBOMER; WATER; DEXPANTHENOL; CENTELLA ASIATICA TRITERPENOIDS; PURSLANE; GLUCOSE

85248-136

Active Ingredient

Clotrimazole 1percent(30mg)

Purpose

Relieves Vaginal ltching

Use

Provides temporary relief from vaginal dryness and discomfort.Moisturizes and soothes the vaginal mucosa.

Warnings

For vaginal use only,not for oral use. The product should not be used as a substitute for medicines and medical devices.

Do not use if you are pregnant, during menstruation, or breastfeeding.Store in a dry and cool place at 20°C-25°C(68°F-77°F)

When Using

·you experience abdominal pain, fever, chills, nausea, vomiting，or foul-smelling discharg. symptoms worsen or do not improve within 7 days.If this is the first time you are experiencing vaginal dryness or discomfort, consult your healthcare provider

Stop Use

·you experience abdominal pain, fever, chills, nausea, vomiting，or foul-smelling discharg. symptoms worsen or do not improve within 7 days.If this is the first time you are experiencing vaginal dryness or discomfort, consult your healthcare provider

Ask Doctor

·you experience abdominal pain, fever, chills, nausea, vomiting，or foul-smelling discharg. symptoms worsen or do not improve within 7 days.If this is the first time you are experiencing vaginal dryness or discomfort, consult your healthcare provider

Keep Oot Of Reach Of Children

Keep out of reach of children, for adults only.

Directions

1.Use one applicator every 2-3 nights ,Wash hands thoroughy before beginning, 2.0pen the foil packet to remove the pre-filed applicator. 3.Twist of the protective cap. 4.Lying down with knees bent,gently insert until comfortable. 5.Slowly push the plunger to dispense the gel6.Remove and properly discard the applicator。7.Rest lying down for a few minutes to let the gel spread.

Inactive ingredients

Purified Water,Dextran,Glucose, Propylene glycol, lnulin,Sodium hyaluronate,Hyaluronic acid, Sodium acetylated hyaluronate,Sodium hyaluronate crosspolymer, Dexpanthenol (Pro-vitamin B5),Rose flower water,Centella asiatica extract, Portulaca oleracea extract,Carbomer,L(+)-Arginine